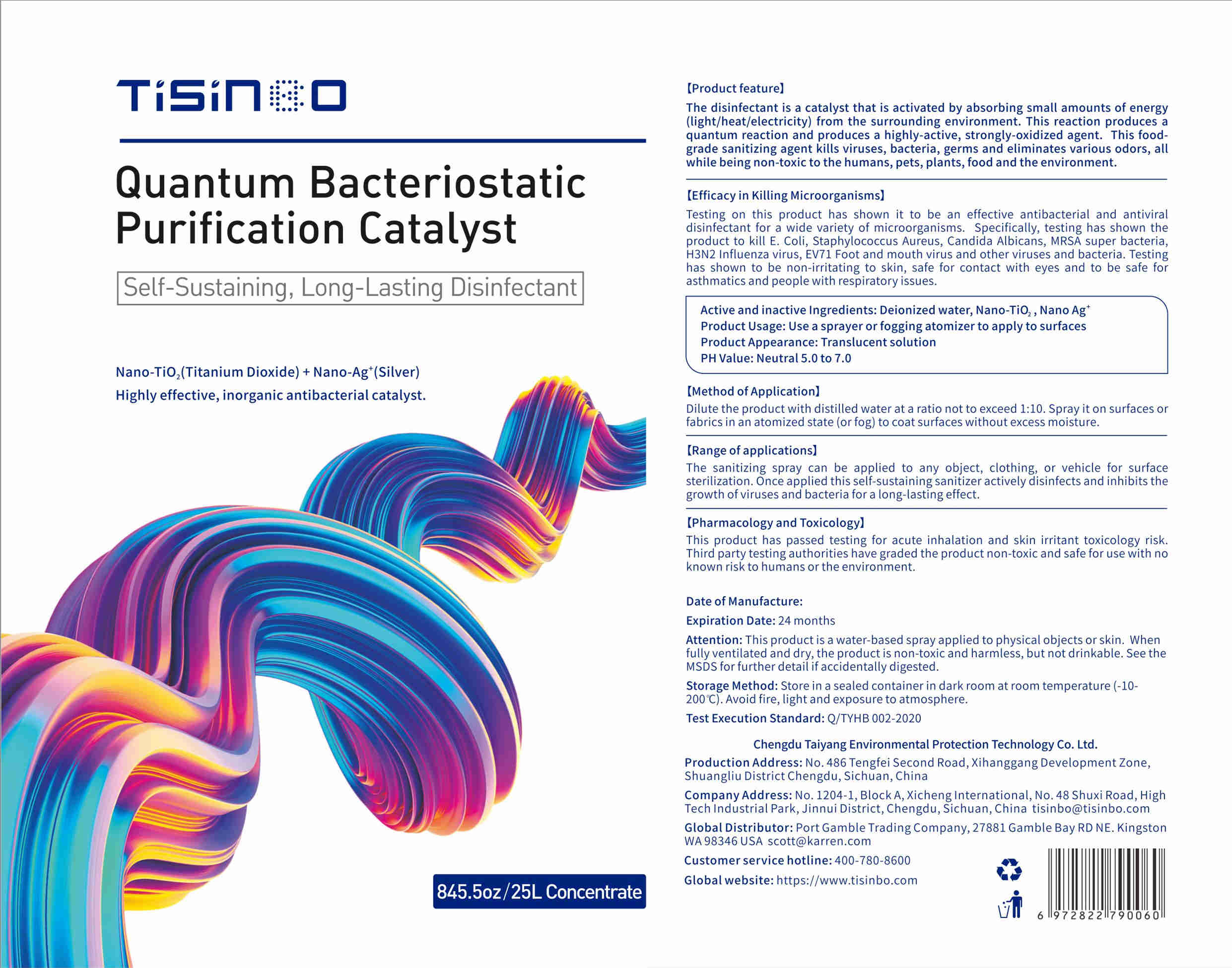 DRUG LABEL: Quantum Bacteriostatic purification catalyst
NDC: 40975-002 | Form: LIQUID
Manufacturer: Chengdu Taiyang Environmental Protection Technology Co., Ltd.
Category: otc | Type: HUMAN OTC DRUG LABEL
Date: 20200617

ACTIVE INGREDIENTS: SILVER 250 g/25000 mL; TITANIUM DIOXIDE 1250 g/25000 mL
INACTIVE INGREDIENTS: WATER

DOSAGE AND ADMINISTRATION

Store at room temperature,avoid fire, light and exposure.

INACTIVE INGREDIENT

deionized water

INDICATIONS AND USAGE

Spray the product on the surface of clothes and keep it dry.

ACTIVE INGREDIENT

Nano-TiO2

nano-Ag

keep out of reach of children

PURPOSE

Disinfection
Sterilization

WARNINGS

This product is water- based, spray wine on. the object or skin surface, and thenfully ventilated and dry the product, this product is non-toxic and hamless, but not drinkable.